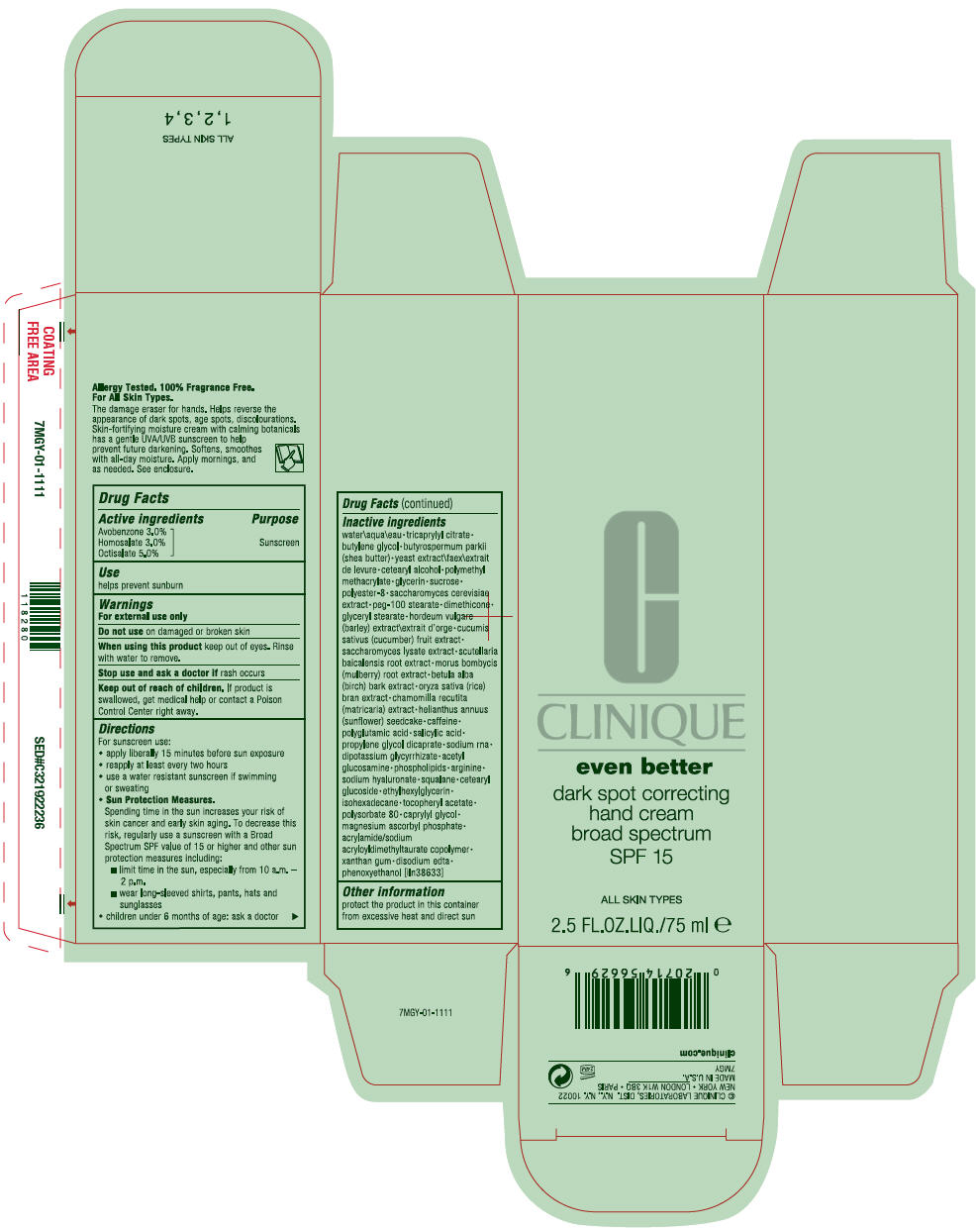 DRUG LABEL: EVEN BETTER DARK SPOT CORRECTING BROAD SPECTRUM 
NDC: 49527-013 | Form: CREAM
Manufacturer: CLINIQUE LABORATORIES LLC
Category: otc | Type: HUMAN OTC DRUG LABEL
Date: 20191111

ACTIVE INGREDIENTS: AVOBENZONE 0.03 g/1 mL; HOMOSALATE 0.03 g/1 mL; OCTISALATE 0.05 g/1 mL
INACTIVE INGREDIENTS: WATER; TRICAPRYLYL CITRATE; BUTYLENE GLYCOL; SHEA BUTTER; YEAST, UNSPECIFIED; CETOSTEARYL ALCOHOL; GLYCERIN; SUCROSE; SACCHAROMYCES CEREVISIAE; PEG-100 STEARATE; DIMETHICONE; GLYCERYL MONOSTEARATE; BARLEY; CUCUMBER; SACCHAROMYCES LYSATE; SCUTELLARIA BAICALENSIS ROOT; MORUS INDICA ROOT; BETULA PUBESCENS BARK; RICE BRAN; MATRICARIA CHAMOMILLA WHOLE; HELIANTHUS ANNUUS SEEDCAKE; CAFFEINE; SALICYLIC ACID; PROPYLENE GLYCOL DICAPRATE; GLYCYRRHIZINATE DIPOTASSIUM; N-ACETYLGLUCOSAMINE; ARGININE; HYALURONATE SODIUM; SQUALANE; CETEARYL GLUCOSIDE; ETHYLHEXYLGLYCERIN; ISOHEXADECANE; .ALPHA.-TOCOPHEROL ACETATE; POLYSORBATE 80; CAPRYLYL GLYCOL; MAGNESIUM ASCORBYL PHOSPHATE; XANTHAN GUM; EDETATE DISODIUM; PHENOXYETHANOL

EVEN BETTER DARK SPOT CORRECTING HAND CREAM BROAD SPECTRUM SPF 15

Drug Facts

Active ingredients

Avobenzone 3.0%
Homosalate 3.0%
Octisalate 5.0%

Purpose

Sunscreen

Use

helps prevent sunburn

Warnings

For external use only

Do not use on damaged or broken skin

When using this product keep out of eyes. Rinse with water to remove.

Stop use and ask a doctor if rash occurs

Keep out of reach of children. If product is swallowed, get medical help or contact a Poison Control Center right away.

Directions

For sunscreen use:

- apply liberally 15 minutes before sun exposure
- reapply at least every two hours
- use a water resistant sunscreen if swimming or sweating
- Sun Protection Measures.
  Spending time in the sun increases your risk of skin cancer and early skin aging. To decrease this risk, regularly use a sunscreen with a Broad Spectrum SPF value of 15 or higher and other sun protection measures including:
  - limit time in the sun, especially from 10 a.m. – 2 p.m.
  - wear long-sleeved shirts, pants, hats and sunglasses
- children under 6 months of age: ask a doctor

Inactive ingredients

water\aqua\eau • tricaprylyl citrate • butylene glycol • butyrospermum parkii (shea butter) • yeast extract\faex\extrait de levure • cetearyl alcohol • polymethyl methacrylate • glycerin • sucrose • polyester-8 • saccharomyces cerevisiae extract • peg-100 stearate • dimethicone • glyceryl stearate • hordeum vulgare (barley) extract\extrait d'orge • cucumis sativus (cucumber) fruit extract • saccharomyces lysate extract • scutellaria baicalensis root extract • morus bombycis (mulberry) root extract • betula alba (birch) bark extract • oryza sativa (rice) bran extract • chamomilla recutita (matricaria) extract • helianthus annuus (sunflower) seedcake • caffeine • polyglutamic acid • salicylic acid • propylene glycol dicaprate • sodium rna • dipotassium glycyrrhizate • acetyl glucosamine • phospholipids • arginine • sodium hyaluronate • squalane • cetearyl glucoside • ethylhexylglycerin • isohexadecane • tocopheryl acetate • polysorbate 80 • caprylyl glycol • magnesium ascorbyl phosphate • acrylamide/sodium acryloyldimethyltaurate copolymer • xanthan gum • disodium edta • phenoxyethanol [iln38633]

Other information

protect the product in this container from excessive heat and direct sun

© CLINIQUE LABORATORIES, DIST. N.Y., N.Y. 10022

PRINCIPAL DISPLAY PANEL - 75 mL Bottle Carton

CLINIQUE

even better

dark spot correcting
hand cream
broad spectrum
SPF 15

ALL SKIN TYPES

2.5 FL.OZ.LIQ./75 ml e